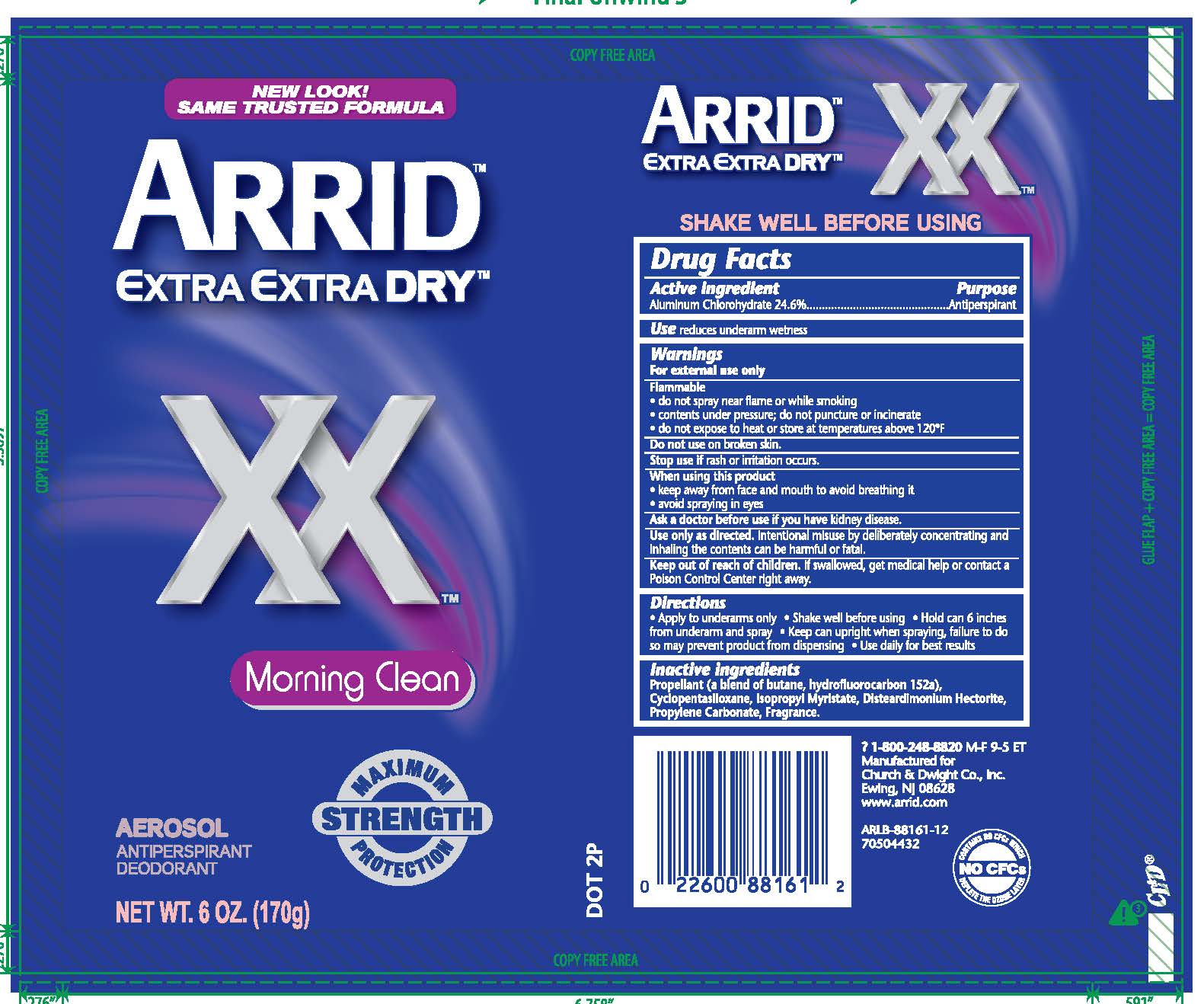 DRUG LABEL: ARRID EXTRA EXTRA DRY XX
NDC: 10237-860 | Form: AEROSOL, SPRAY
Manufacturer: Church & Dwight Co., Inc.
Category: otc | Type: HUMAN OTC DRUG LABEL
Date: 20250611

ACTIVE INGREDIENTS: ALUMINUM CHLOROHYDRATE 246 mg/1 g
INACTIVE INGREDIENTS: BUTANE; 1,1-DIFLUOROETHANE; CYCLOMETHICONE 5; ISOPROPYL MYRISTATE; HECTORITE; PROPYLENE CARBONATE

ARRID XX Morning Clean Spray

Active ingredient

Aluminum Chlorohydrate

Purpose

Antiperspirant

INDICATIONS AND USAGE

Use reduces underarm wetness

Warnings

For external use only

Flammable

- do not spray near flame or while smoking
- contents under pressure do not puncture or incinerate
- do not expose to heat or store at temperatures above 120F

Do not use on broken skin.

Stop use if rash or irritation occurs.

When using this product

- keep away from face and mouth to avoid breathing it
- avoid spraying in eyes

Ask a doctor before use if you have kidney disease.

Use only as directed. Intentional misuse by deliberately concentrating and inhaling the contents can be harmful or fatal.

Keep out of reach of children. If swallowed, get medical help or contact a Poison Control Center right away.

Directions

- apply to underarms only
- shake well, hold can 6 inches from underarm and spray
- use daily for best results

Inactive ingredients

Propellant (a blend of butane, hydrofluorocarbon 152a), Cyclopentasiloxane, Isopropyl Myristate, Disteardimonium Hectorite, Propylene Carbonate, Fragrance.

PACKAGE LABEL

NEW LOOK!

SAME TRUSTED FORMULA

ARRID

EXTRA EXTRA DRY

XX

Morning Clean

MAXIMUM STRENGTH PROTECTION

AEROSOL ANTIPERSPIRANT DEODORANT

NEW WT. 6.0 OZ. (170g)